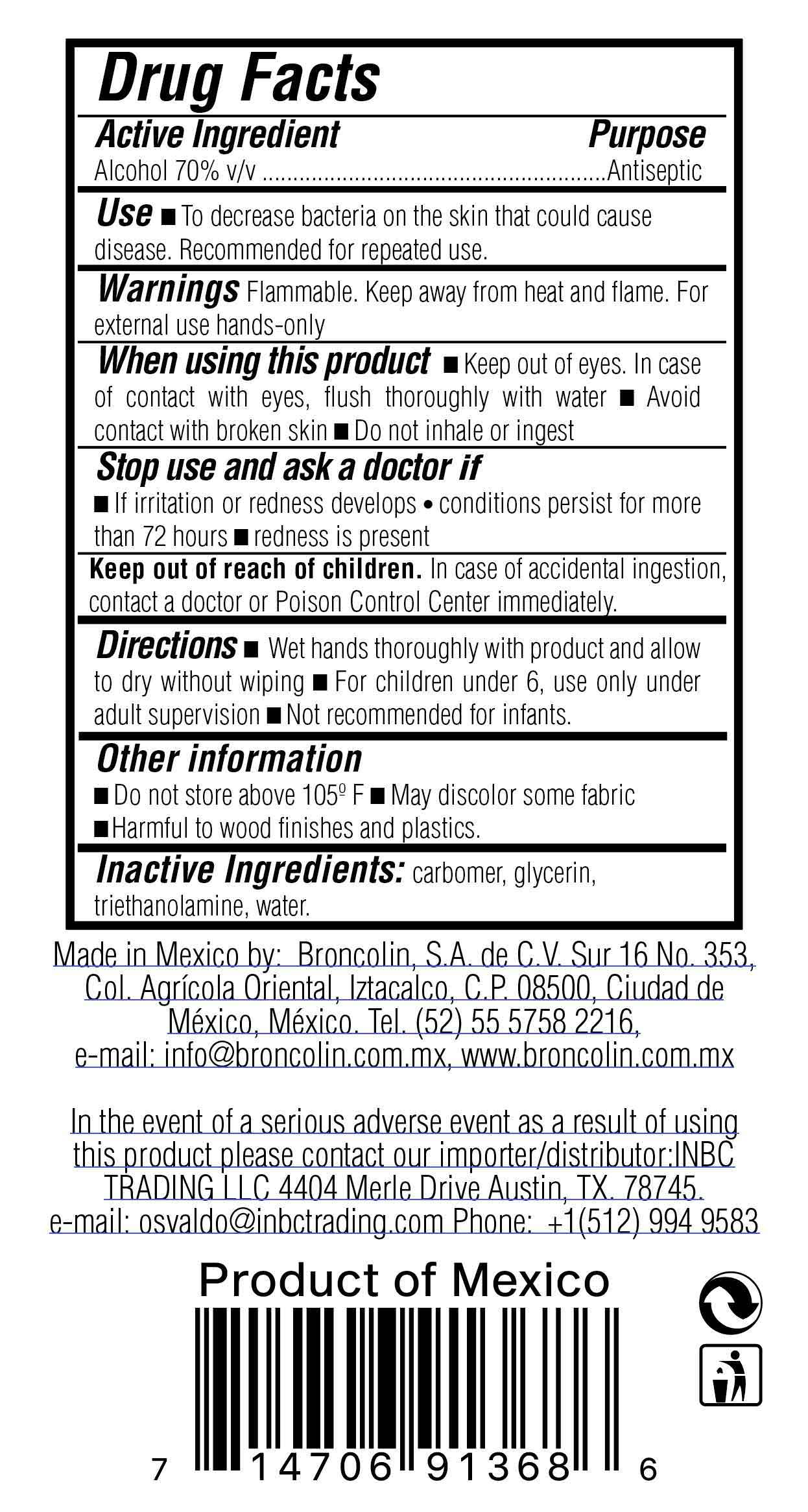 DRUG LABEL: Hand Sanitizer
NDC: 62583-020 | Form: GEL
Manufacturer: Broncolin, S.A. de C.V
Category: otc | Type: HUMAN OTC DRUG LABEL
Date: 20200420

ACTIVE INGREDIENTS: ALCOHOL 70 mL/100 mL
INACTIVE INGREDIENTS: GLYCERIN; TROLAMINE; WATER; CARBOMER HOMOPOLYMER, UNSPECIFIED TYPE

Herbacil Hand Sanitizer

Active Ingredient

Alcohol 70%

Purpose

Antiseptic

Use

■ To decrease bacteria on the skin that could cause disease. Recommended for repeated use.

Warnings

Flammable. Keep away from fire & flame. For external use hands only

When using this product

■ Keep out of eyes. In case of contact with eyes, flush thoroughly with water ■ Avoid contact with broken skin ■ Do not inhale or ingest

Stop use and ask a doctor if

■ irritation or redness develops ■ conditions persist for more than 72 hours ■ redness is present

Keep out of reach of children

In case of accidental ingestion, contact a doctor or Poison Control Center immediately.

Directions

■ Wet hands throughhly with product,and allow to dry without wiping ■ For children under 6, use only with adult supervision ■ Not recommended for infants

Other information

■ Do not store above105ºF ■ May discolor some fabrics ■ Harmful to wood finishes and plastics

Inactive Ingredients

carbomer, glycerin, triethanolamine, water